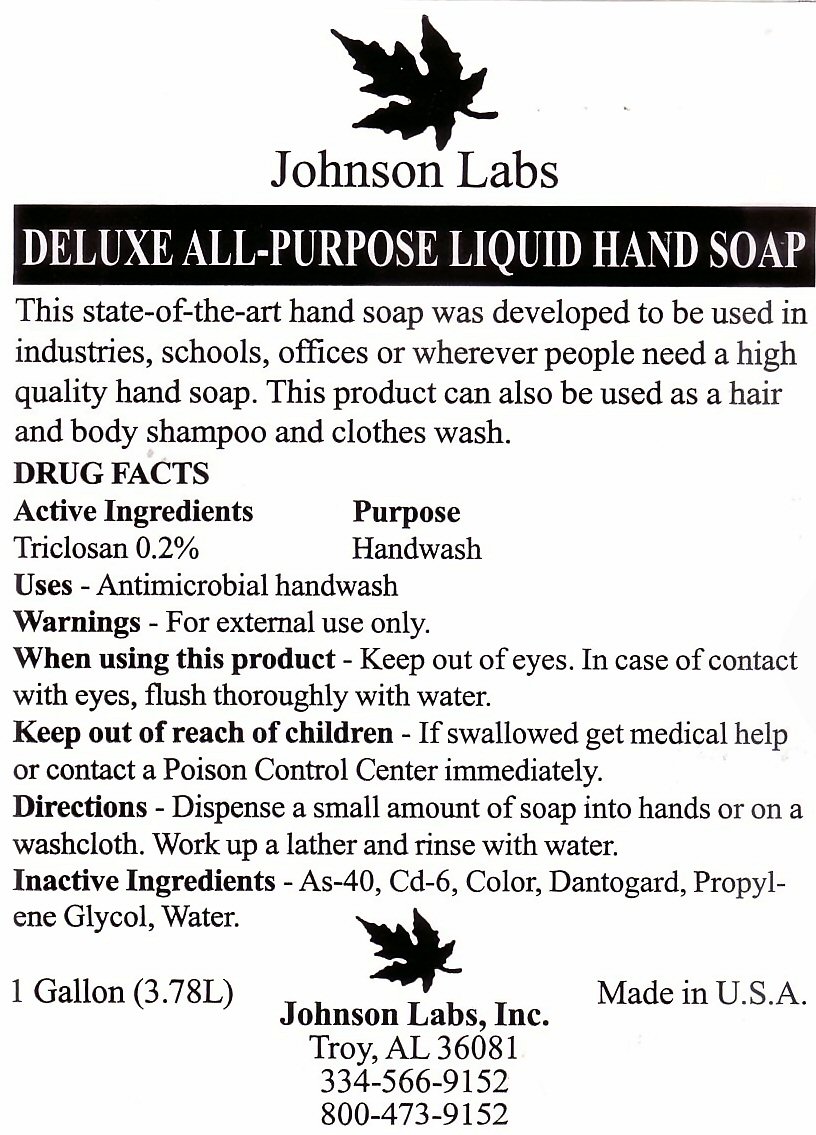 DRUG LABEL: DELUXE ALL-PURPOSE 
NDC: 59854-301 | Form: LIQUID
Manufacturer: Johnson Labs, Inc.
Category: otc | Type: HUMAN OTC DRUG LABEL
Date: 20120402

ACTIVE INGREDIENTS: TRICLOSAN 7.57 mL/3.78 L
INACTIVE INGREDIENTS: SODIUM C14-16 OLEFIN SULFONATE; COCO DIETHANOLAMIDE; DMDM HYDANTOIN; PROPYLENE GLYCOL; WATER 

Active Ingredient

Drug Facts Active Ingredients Triclosan 0.2 %

Purpose

Purpose Handwash

Keep out of reach of children - If swallowed get medical help or contact a Poison Control Center immediately.

Uses

Antimicrobial handwash.

Warnings

Warnings - For external use only.

When using this product - Keep out of eyes. In case of contact with eyes, flush thoroughly with water.

Directions

Directions - Dispense a small amount of soap into hands or on a washcloth. Work up a lather and rinse with water.

Inactive Ingredients

Inactive Ingredients - As-40, Cd-6, Color, Dantogard, Propylene Glycol, Water.

Package Label

Johnson Labs DELUXE ALL-PURPOSE LIQUID HAND SOAP

This state-of-the-art hand soap was developed to be used in industries, schools, offices or wherever people need a high quality hand soap. This product can also be used as a hair and body shampoo and clothes wash.

1 Gallon (3.78L) made in U.S.A. Johnson Labs, Inc. Troy, AL 36081 334-566-9152 800-473-9152